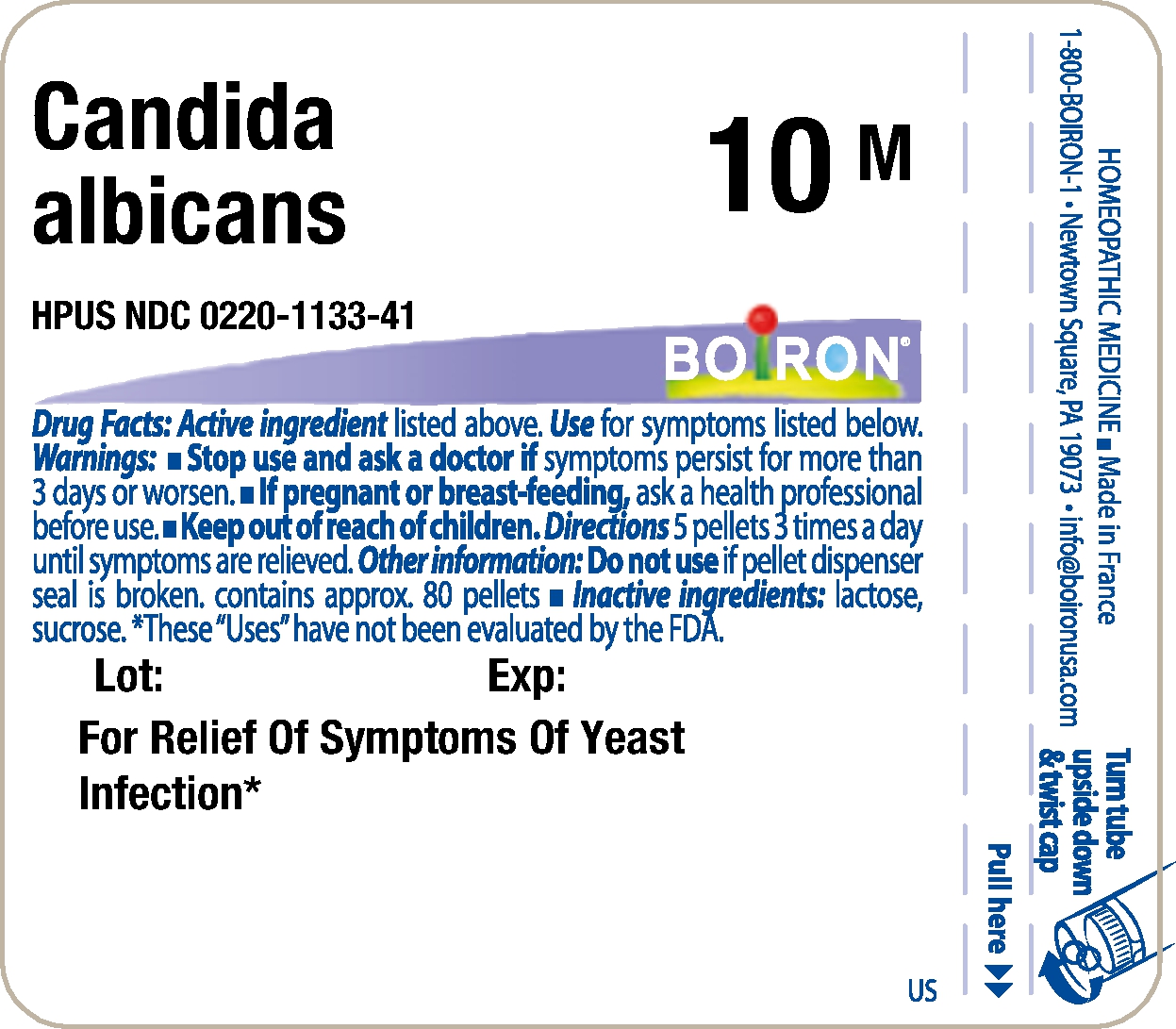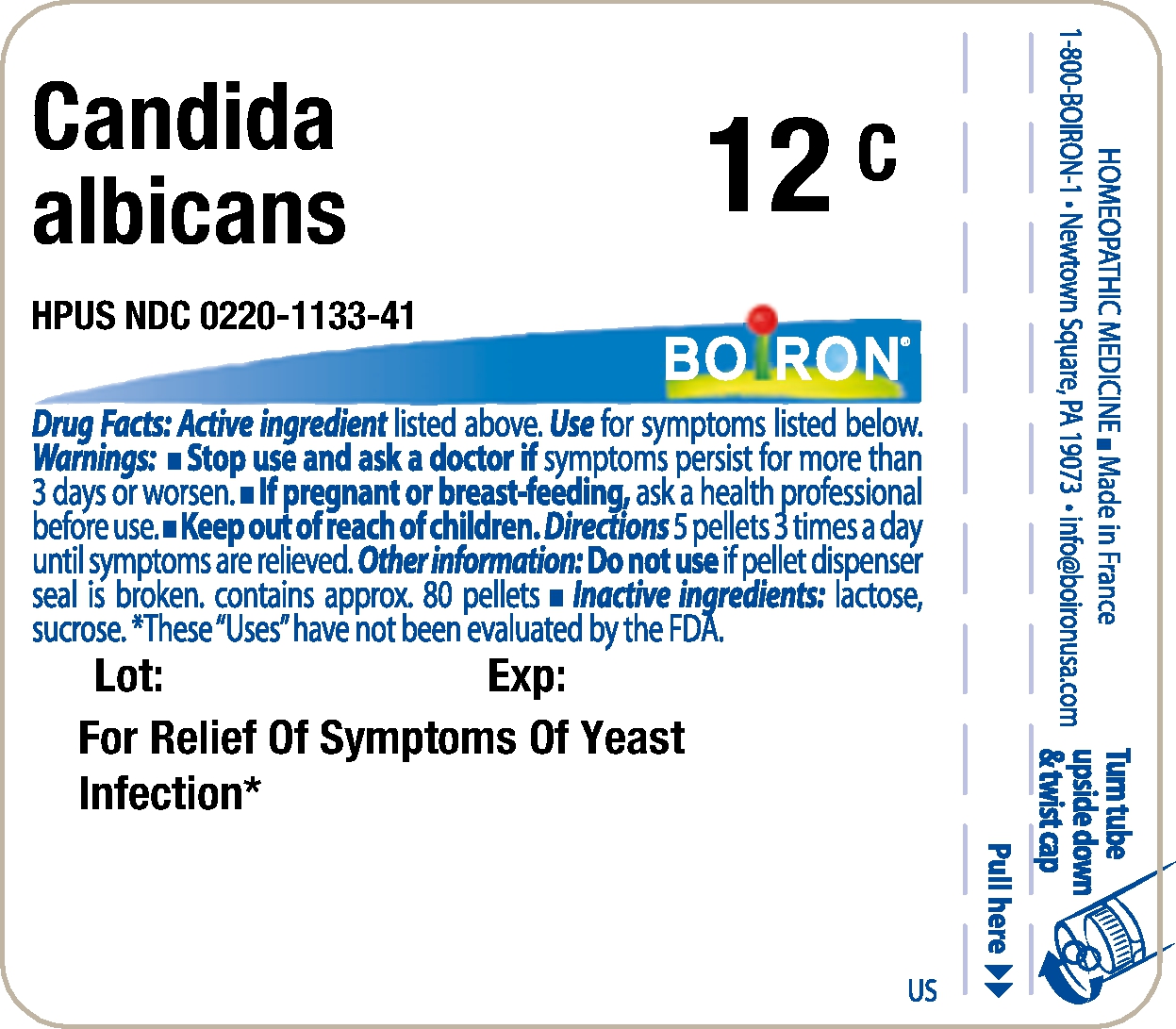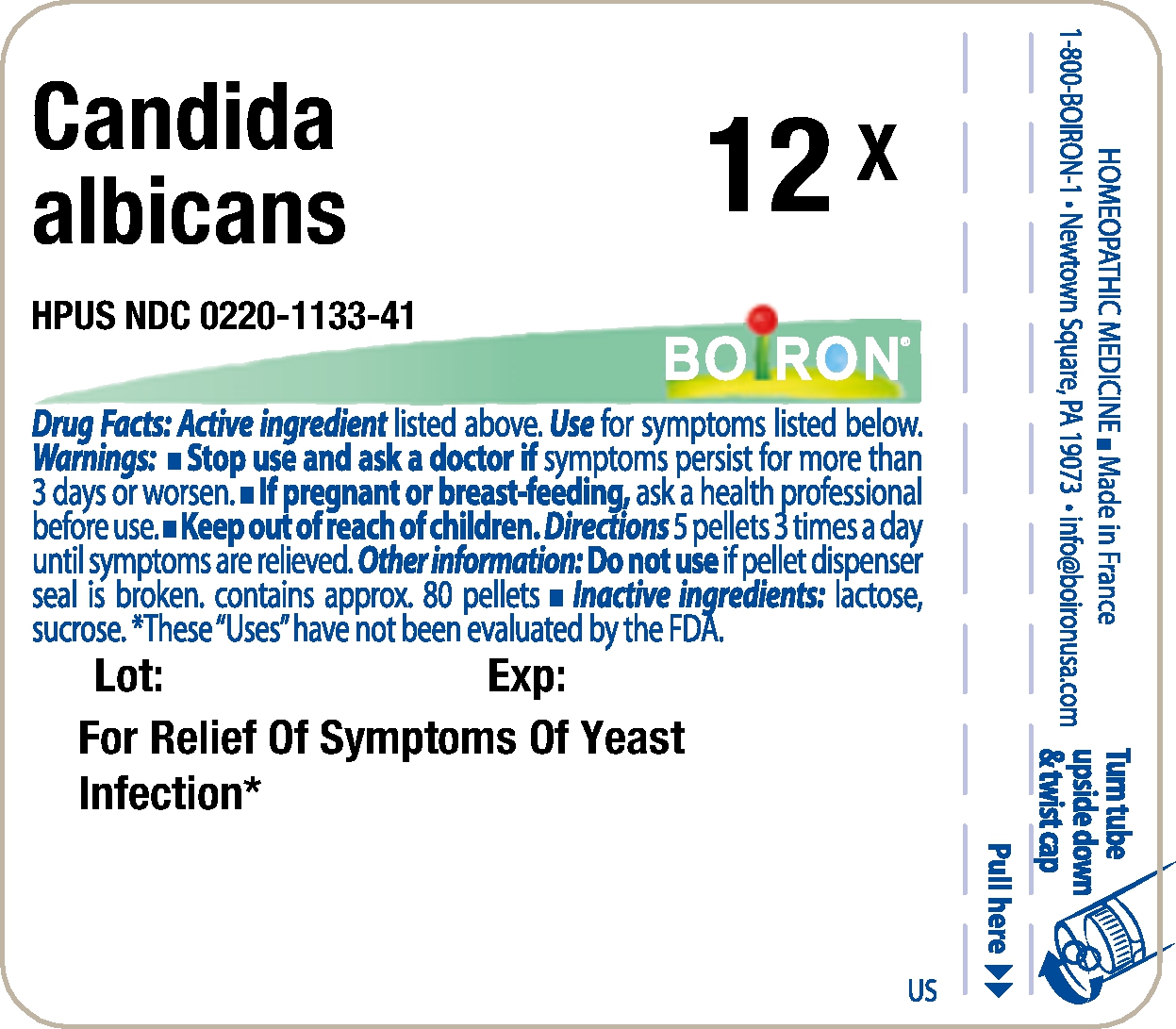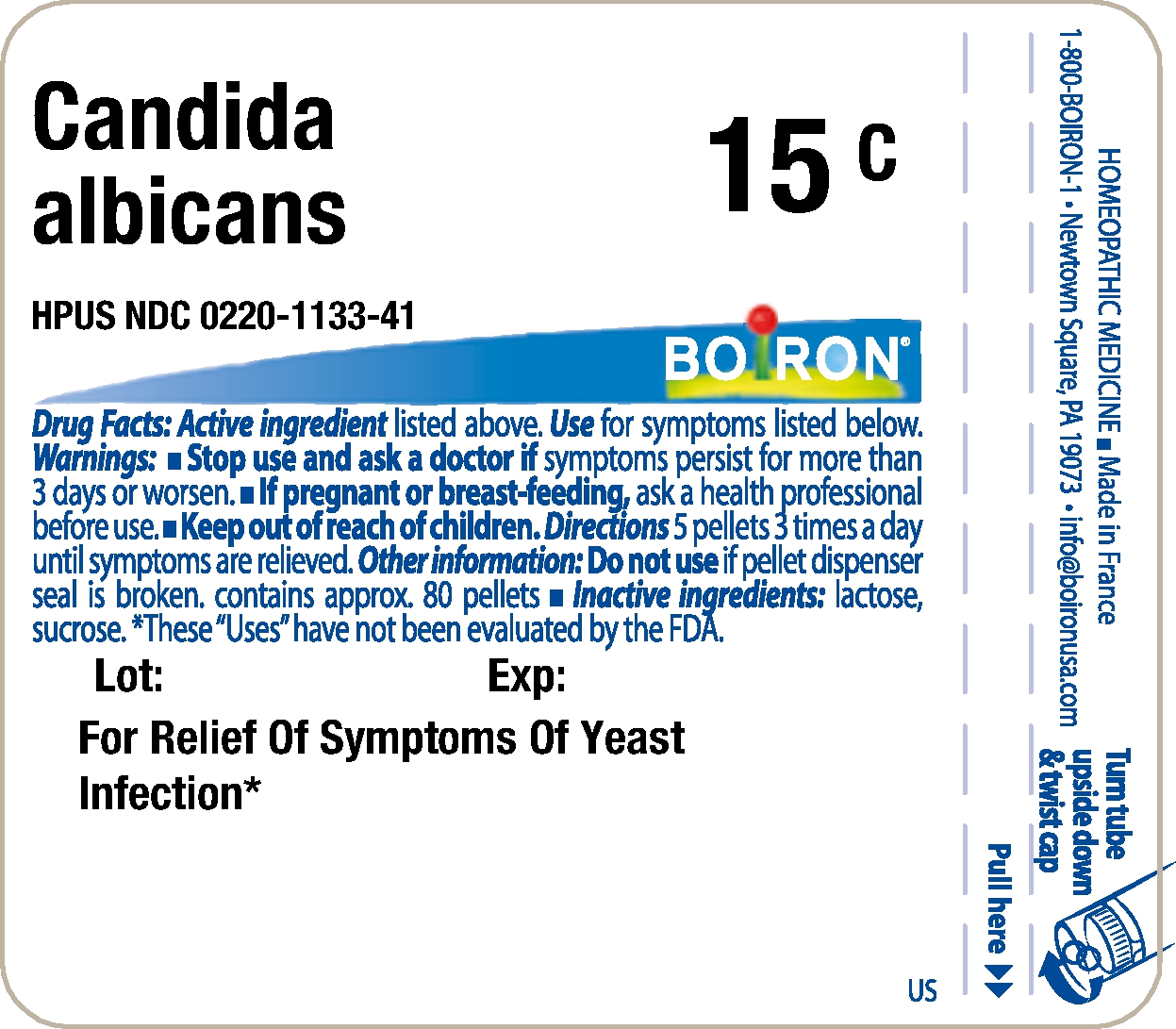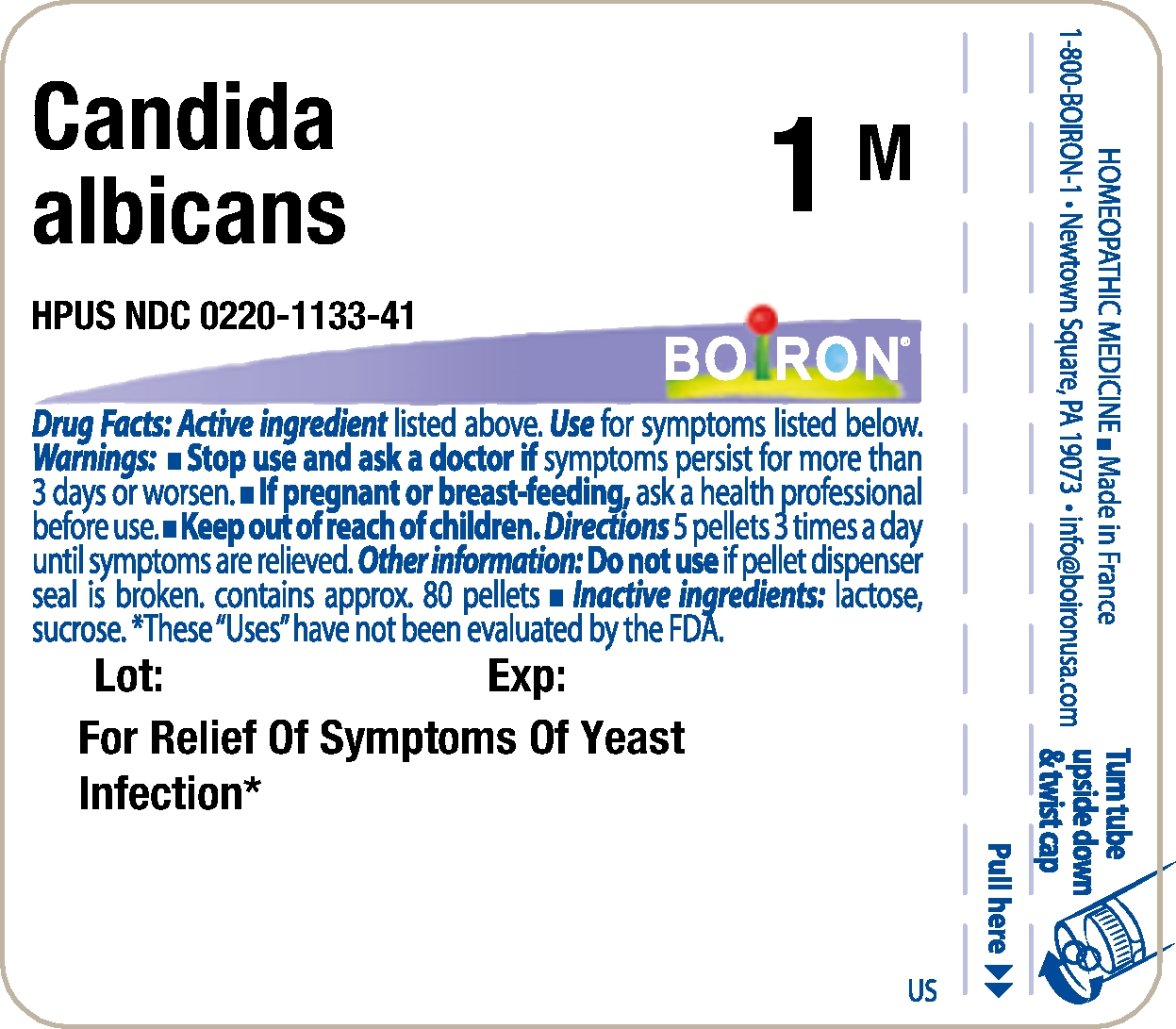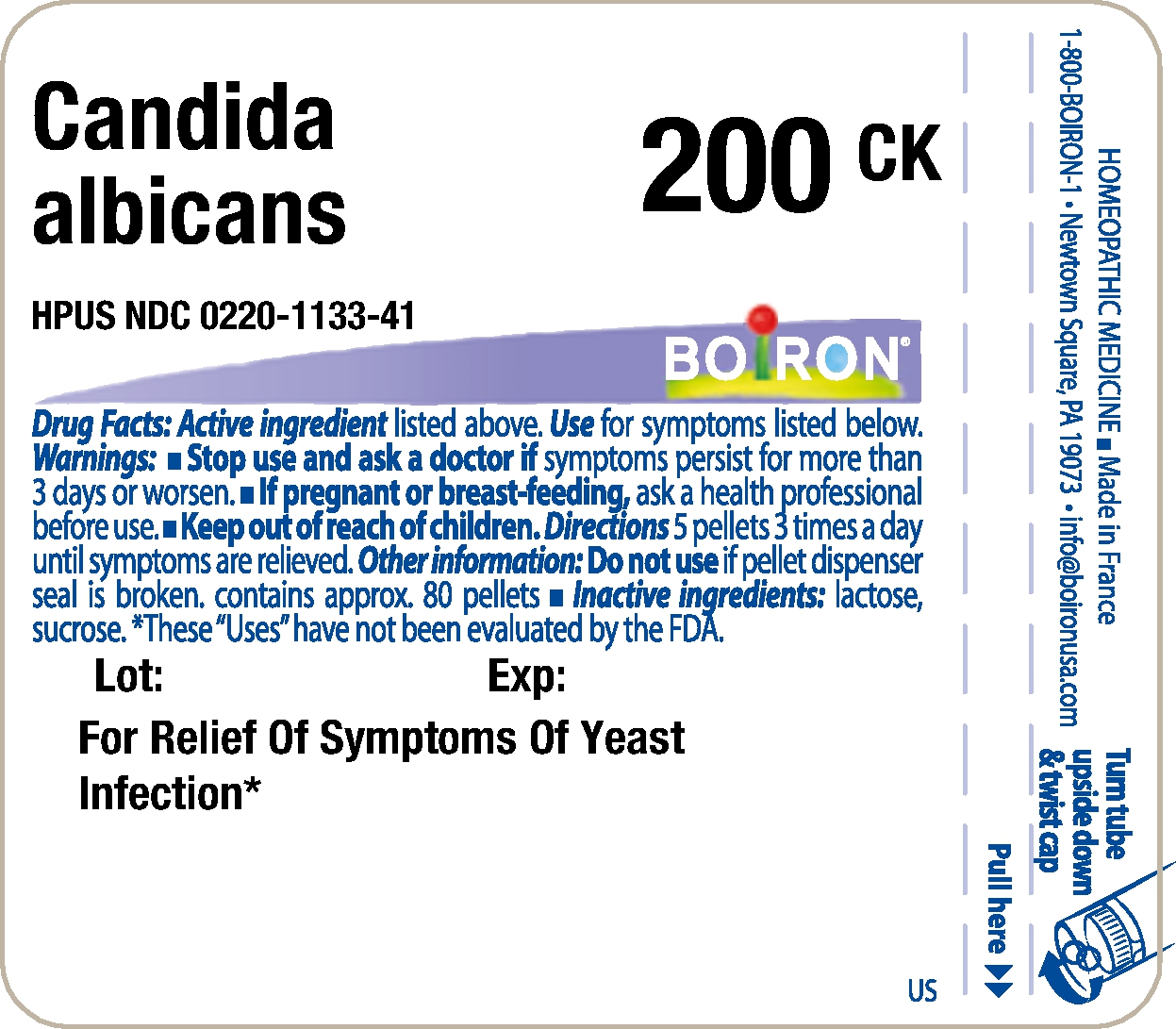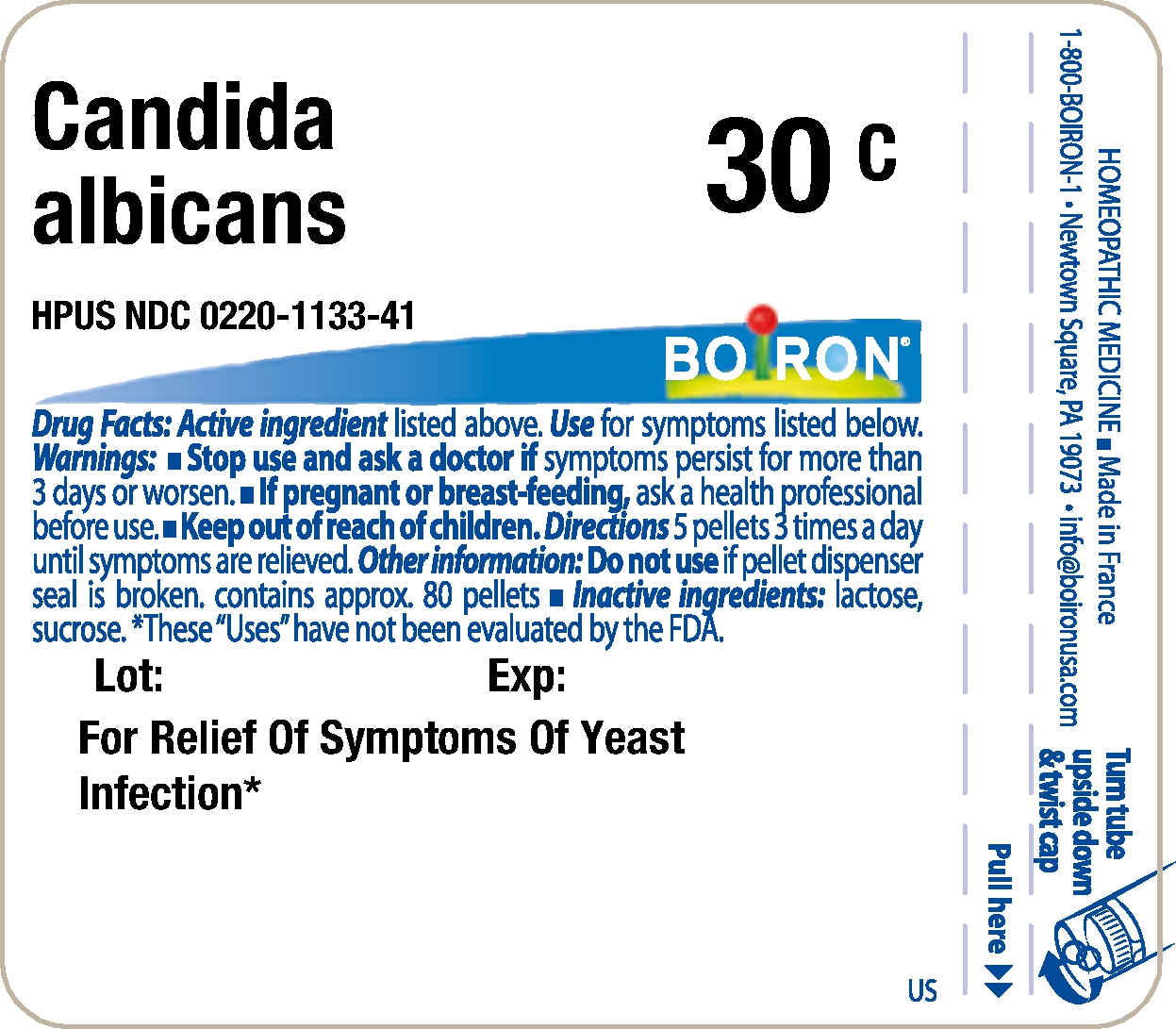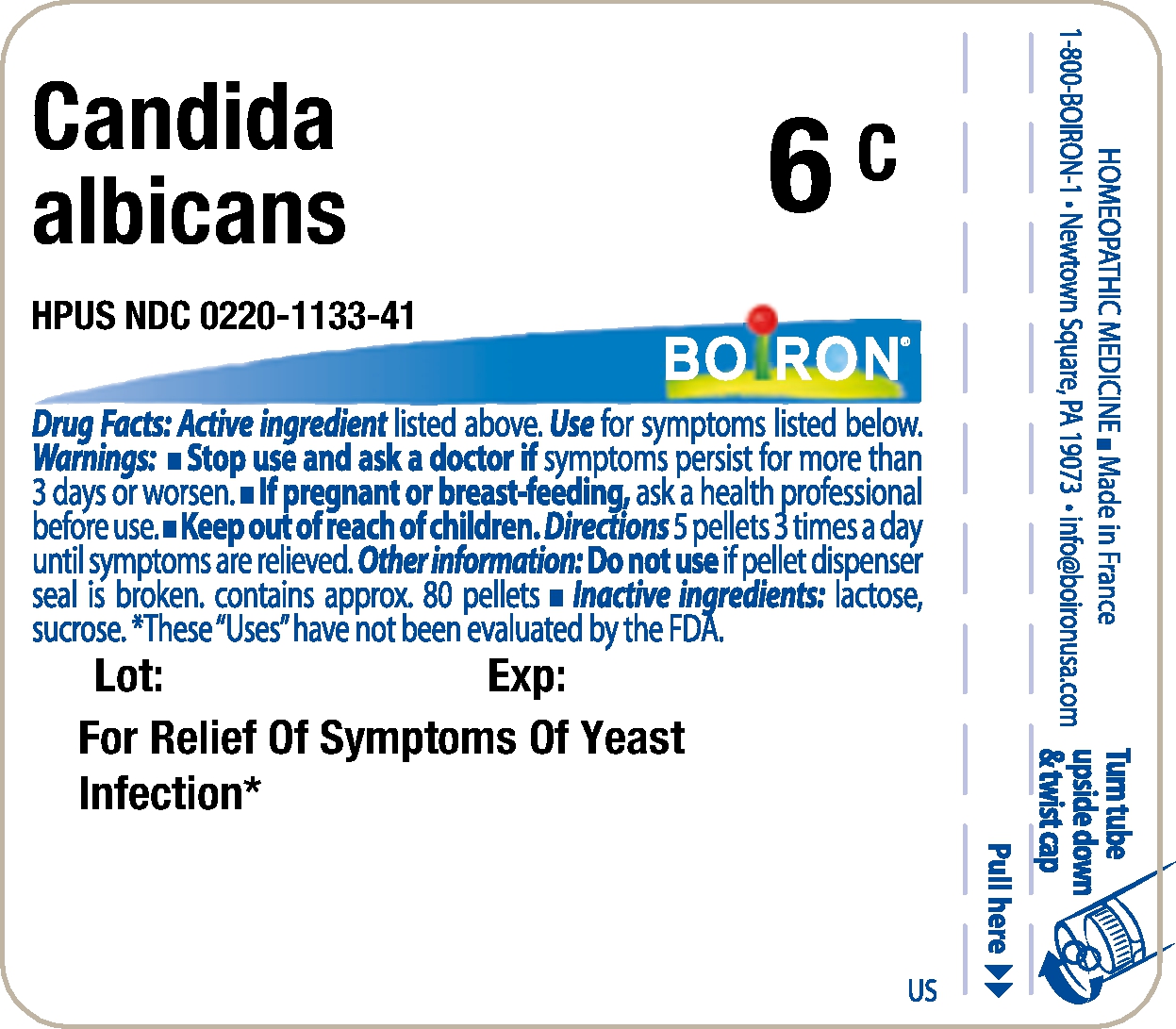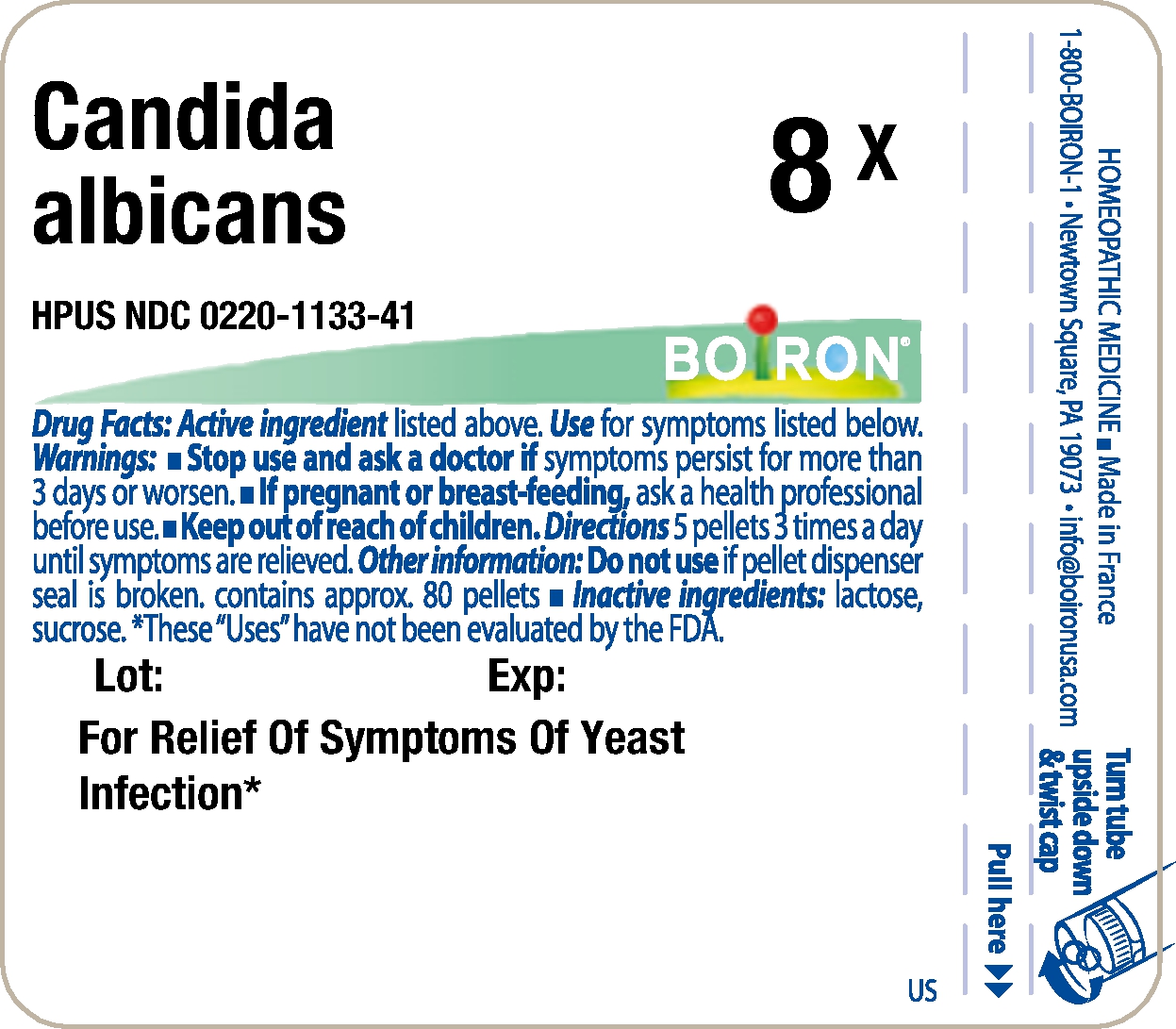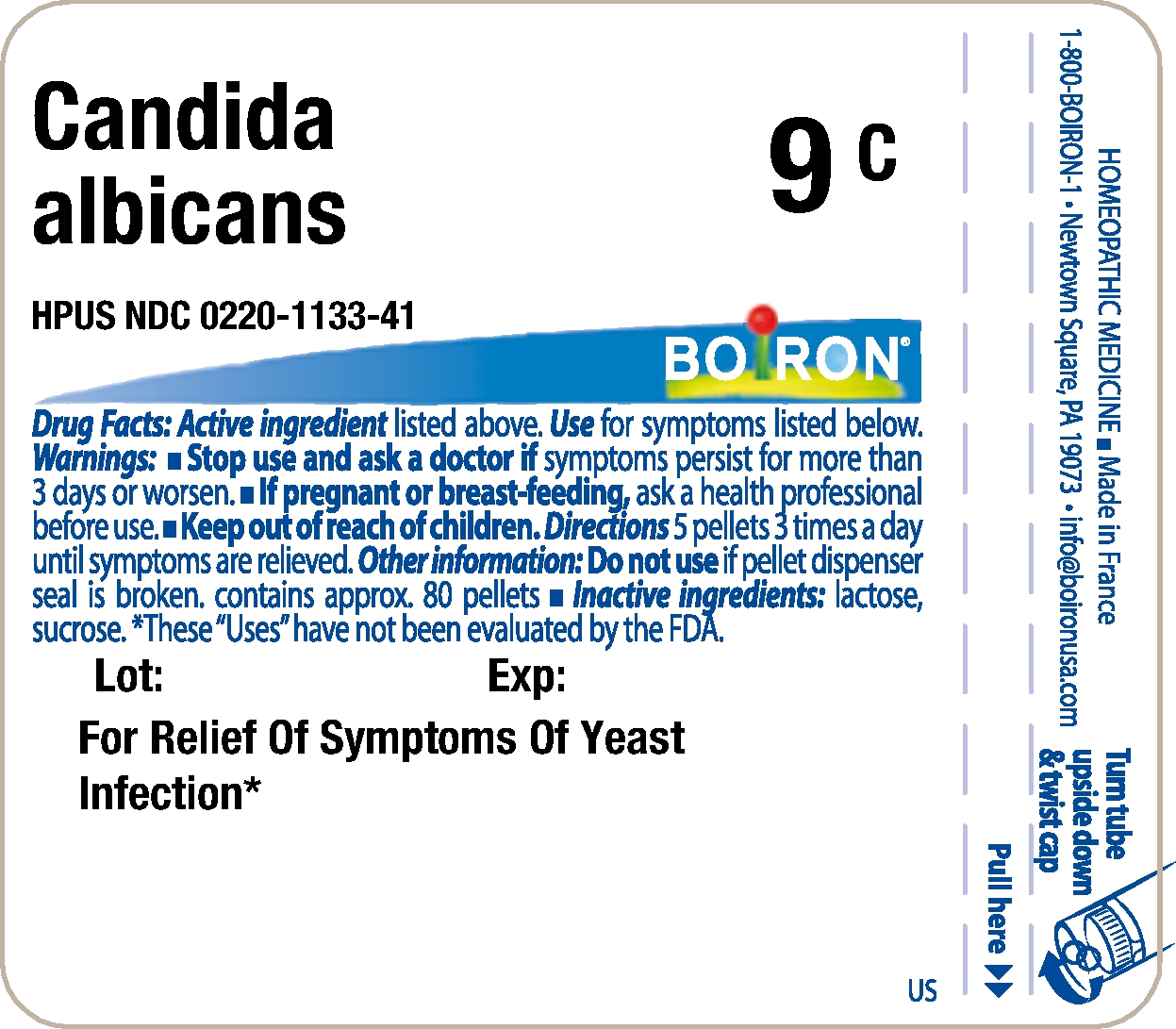 DRUG LABEL: Candida albicans
NDC: 0220-1133 | Form: PELLET
Manufacturer: Laboratoires Boiron
Category: homeopathic | Type: HUMAN OTC DRUG LABEL
Date: 20231109

ACTIVE INGREDIENTS: CANDIDA ALBICANS 8 [hp_X]/1 1
INACTIVE INGREDIENTS: SUCROSE; LACTOSE

Candida albicans

Active Ingredients

Candida albicans HPUS
8X, 12X, 6C, 9C, 12C, 15C, 30C, 200CK, 1M, 10M

Use

For Relief Of Symptoms Of Yeast Infection*

Warnings

Stop use and ask a doctor if

symptoms persist for more than 3 days or worsen.

If pregnant or breast-feeding,

ask a health professional before use.

Directions

5 pellets 3 times a day until symptoms are relieved.

Other information

Do not use if pellet dispenser seal is broken.
contains approx. 80 pellets

Inactive ingredients

lactose, sucrose

Questions, Comments?

1-800-BOIRON-1
Newtown Square, PA 19073-3267
info@boironusa.com

*

These "Uses" have not been evaluated by the FDA.